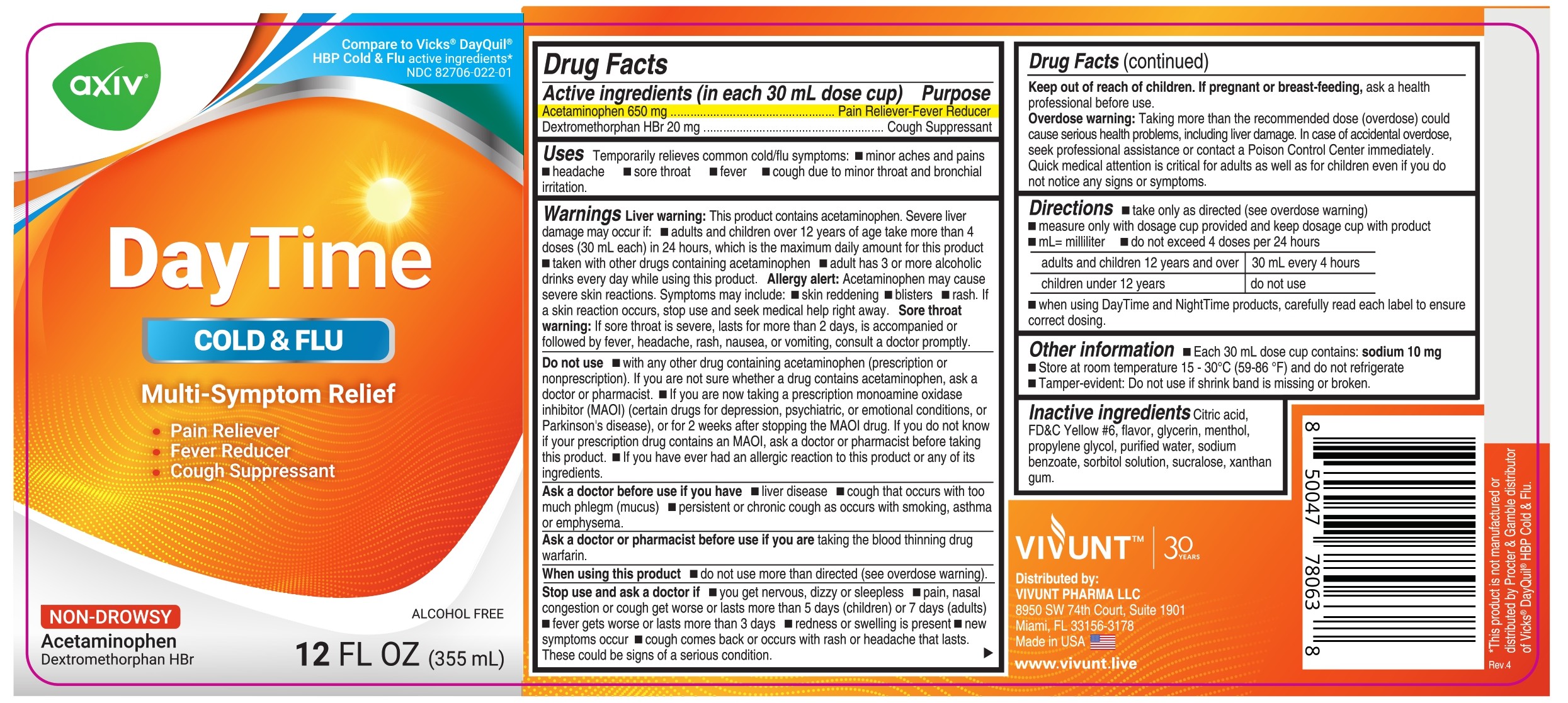 DRUG LABEL: AXIV DayTime - Liquid
NDC: 82706-022 | Form: LIQUID
Manufacturer: VIVUNT PHARMA LLC
Category: otc | Type: HUMAN OTC DRUG LABEL
Date: 20250917

ACTIVE INGREDIENTS: ACETAMINOPHEN 650 mg/30 mL; DEXTROMETHORPHAN HYDROBROMIDE 20 mg/30 mL
INACTIVE INGREDIENTS: CITRIC ACID MONOHYDRATE; GLYCERIN; FD&C YELLOW NO. 6; MENTHOL, UNSPECIFIED FORM; WATER; SODIUM BENZOATE; PROPYLENE GLYCOL; SUCRALOSE; SORBITOL SOLUTION; XANTHAN GUM

AXIV - DayTime Cold & Flu - Liquid

Drug Facts

ACTIVE INGREDIENT

PURPOSE

Active ingredients (in each 30 mL dose cup) | Purpose
Acetaminophen 650 mg | Pain reliever/fever reducer
Dextromethorphan HBr 20 mg | Cough suppressant

Uses

Temporarily relieves common cold/flu symptoms:

- minor aches and pains
- headache
- sore throat
- fever
- cough due to minor throat and bronchial irritation

Warnings

Liver warning

This product contains acetaminophen. Severe liver damage may occur if you take

- adults and children over 12 years of age take more than 4 doses (30 mL each) in 24 hours, which is the maximum daily amount for this product
- taken with other drugs containing acetaminophen
- adult has 3 or more alcoholic drinks every day while using this product

Allergy alert

Acetaminophen may cause severe skin reactions. Symptoms may include:

- skin reddening
- blisters
- rash

If a skin reaction occurs, stop use and seek medical help right away

Sore throat warning

If sore throat is severe, lasts for more than 2 days, is accompanied or followed by fever, headache, rash, nausea, or vomiting, consult a doctor promptly.

Do not use

- with any other drug containing acetaminophen (prescription or nonprescription). If you are not sure whether a drug contains acetaminophen, ask a doctor or pharmacist.
- if you are now taking a prescription monoamine oxidase inhibitor (MAOI) (certain drugs for depression, psychiatric, or emotional conditions, or Parkinson's disease), or for 2 weeks after stopping the MAOI drug. If you do not know if your prescription drug contains an MAOI, ask a doctor or pharmacist before taking this product.
- if you have ever had an allergic reaction to this product or any of its ingredients

Ask a doctor before use if you have

- liver disease
- cough that occurs with too much phlegm (mucus)
- persistent or chronic cough as occurs with smoking, asthma, or emphysema

Ask a doctor or pharmacist before use if you are

taking the blood thinning drug warfarin.

When using this product

do not use more than directed (see overdose warning)

Stop use and ask a doctor if

- you get nervous, dizzy or sleepless
- pain or cough gets worse or lasts more than 7 days
- fever gets worse or lasts more than 3 days
- redness or swelling is present
- new symptoms occur
- cough comes back or occurs with rash or headache that lasts.

These could be signs of a serious condition

Keep out of reach of children.

If pregnant or breast-feeding

ask a health professional before use.

Overdose warning

Taking more than the recommended dose (overdose) could cause seriuos health problems, including liver damage. In case of accidental overdose, seek professional assistance or contact a Poison Control Center immediately. Quick medical attention is critical for adults as well as for children even if you do not notice any signs or symptoms.

Directions

- take only as directed (see overdose warning)
- measure only with dosage cup provided and keep dosage cup with product
- mL = milliliter
- do not exceed 4 doses per 24 hours
- when using DayTime and NightTime products, carefully read each label to ensure correct dosing

adults and children 12 years and over | 30 mL every 4 hours
children under 12 years | do not use

Other information

- Each 30 mL dose cup contains: sodium 10 mg
- Store at room temperature 15 - 30°C (59 - 86°F) and do not refrigerate
- Tamper evident: Do not use if shrink band is missing or broken

Inactive ingredients

Citric acid, FD&C Yellow #6, flavor, glycerin, menthol, propylene glycol, purified water, sodium benzoate, sorbitol solution, sucralose, xanthan gum.

Distributed by:

VIVUNT PHARMA LLC
8950 SW 74th. Court. Suite 1901

Miami, FL 33156-3178

Made in USA

www.vivunt.live

PRINCIPAL DISPLAY PANEL

Compare to

VICKS ® DayQuil®

Cold&Flu active ingredients*

NDC 82706-022-01

AXIV - DayTime

COLD&FLU

Multi-Symptom Relief

- Pain Reliever
- Fever Reducer
- Cough Suppressant
- Nasal Decongestant

Non-Drowsy

Acetaminophen, Dextromethorphan HBr

12 FL OZ (355 mL)

*This product is not manufactured or distributed by The Procter &Gamble Company, owner of the registered trademarks Vicks® DayQuil®.